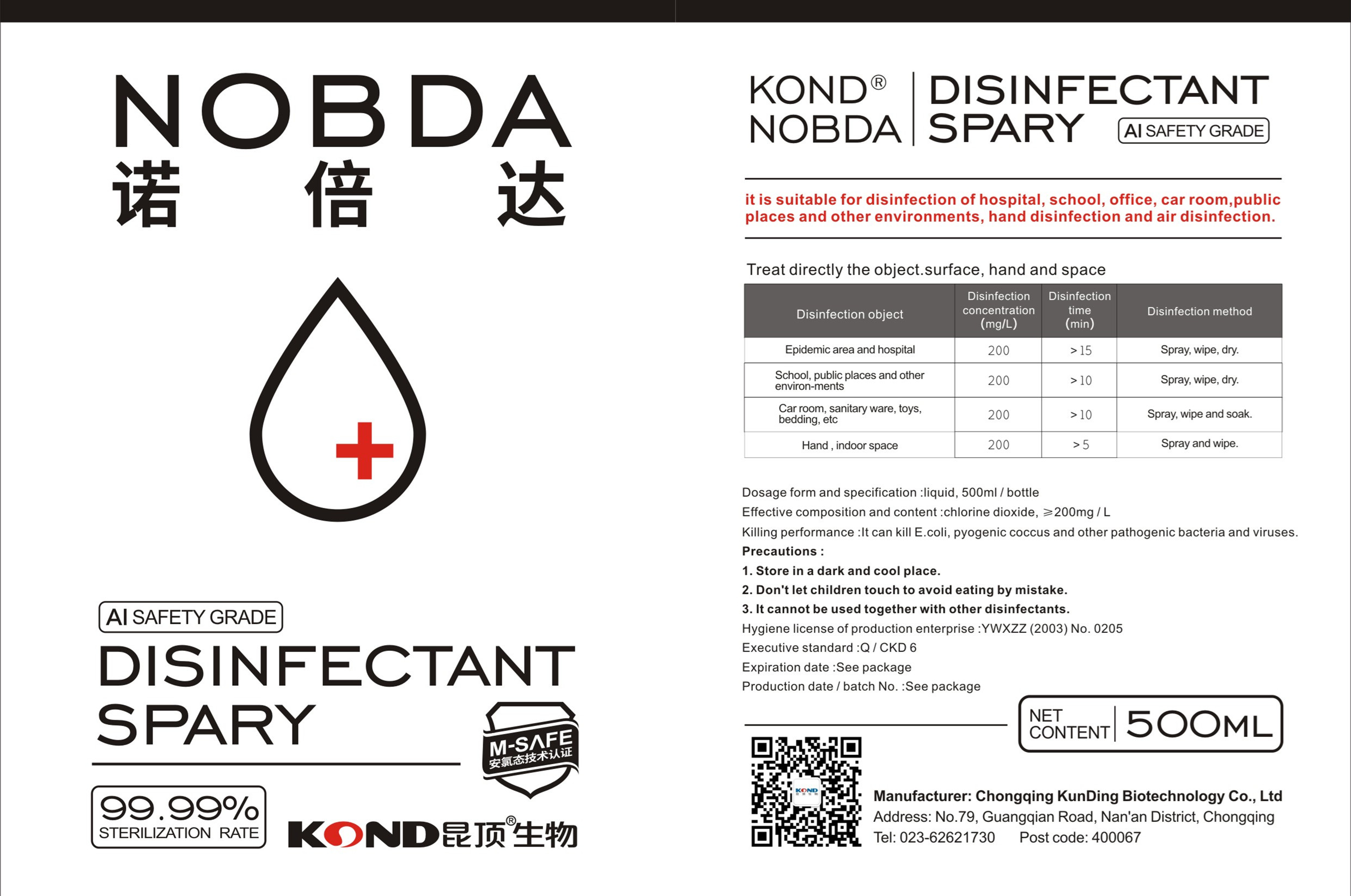 DRUG LABEL: Nobda disinfectant
NDC: 54520-001 | Form: LIQUID
Manufacturer: Chongqing Kunding Biologic Technology Co., Ltd.
Category: otc | Type: HUMAN OTC DRUG LABEL
Date: 20200407

ACTIVE INGREDIENTS: CHLORINE DIOXIDE 0.115 mg/500 mL
INACTIVE INGREDIENTS: WATER

DOSAGE AND ADMINISTRATION

Press the button two times three times

INACTIVE INGREDIENT

water

ACTIVE INGREDIENT

Chlorine dioxide

keep out of children

PURPOSE

it can kill E .coli, pyogenic coccus and other pathogenic bacteria and viruses.

WARNINGS

1. Store in a dark and cool place.
2. Don't let children touch to avoid eating by mistake.
3. It cannot be used together with other disinfectants.

INDICATIONS AND USAGE

直接对待物体。表面，手和空间